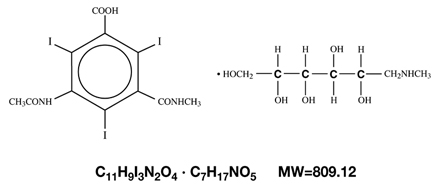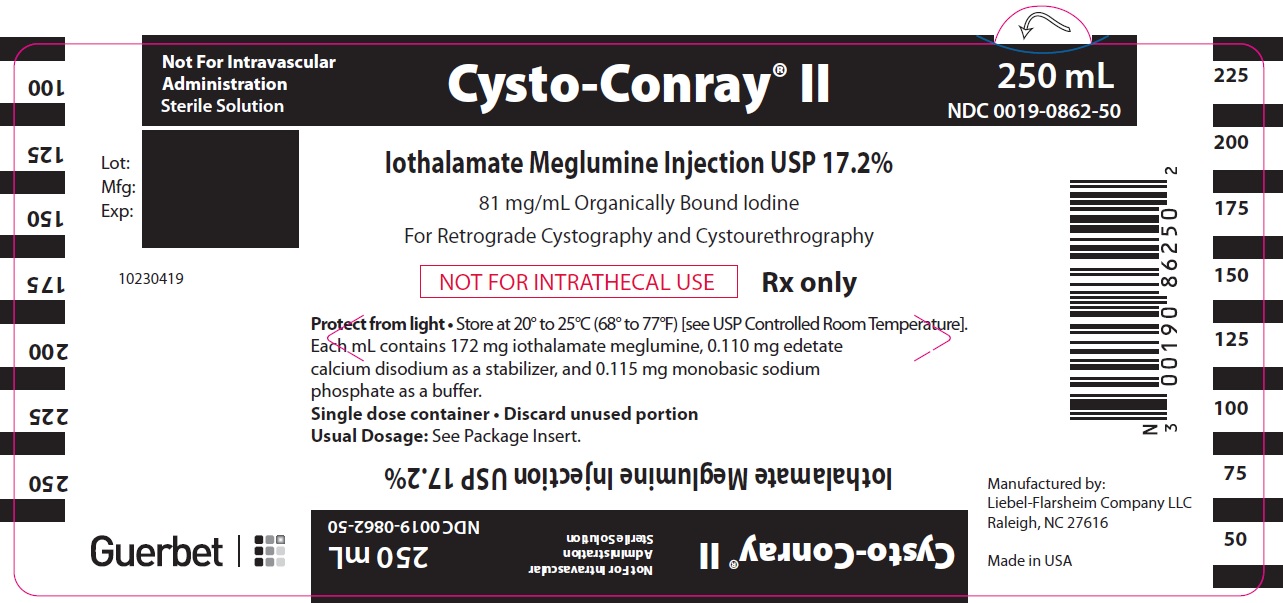 DRUG LABEL: Cysto-Conray II
NDC: 0019-0862 | Form: INJECTION
Manufacturer: Liebel-Flarsheim Company LLC
Category: prescription | Type: HUMAN PRESCRIPTION DRUG LABEL
Date: 20201231

ACTIVE INGREDIENTS: IOTHALAMATE MEGLUMINE 172 mg/1 mL
INACTIVE INGREDIENTS: EDETATE CALCIUM DISODIUM; SODIUM PHOSPHATE, MONOBASIC, UNSPECIFIED FORM

August 2017
Cysto-Conray® II
[Iothalamate Meglumine Injection USP 17.2%]
Rx only

BOXED WARNING

NOT FOR INTRAVASCULAR ADMINISTRATION

NOT FOR INTRATHECAL USE

DESCRIPTION

Cysto-Conray II is a sterile aqueous solution intended for instillation as a diagnostic radiopaque medium. Cysto-Conray II contains 17.2% w/v iothalamate meglumine which is 1-Deoxy-1-(methylamino)-D-glucitol 5-acetamido-2,4,6-triiodo-N-methylisophthalamate (salt) and has the following structural formula:

Each milliliter of Cysto-Conray II contains 172 mg of iothalamate meglumine, equivalent to 81 mg (8.1% w/v) of organically bound iodine, 0.110 mg edetate calcium disodium as a stabilizer and 0.115 mg of monobasic sodium phosphate as a buffer.

Cysto-Conray II is hypertonic under conditions of use and is supplied in containers from which the air has been displaced by nitrogen. The pH of Cysto-Conray II is
6.6 to 7.6.

CLINICAL PHARMACOLOGY

The most important characteristic of contrast media is the iodine content. The relatively high atomic weight of iodine contributes sufficient radiodensity for radiographic contrast.

Following instillation by sterile catheter, Cysto-Conray II provides for visualization of the lower urinary tract. Clinical literature reports indicate that routinely less than 1 percent of a retrograde urographic radiopaque is absorbed systemically, however, as much as 12 percent absorption was observed with pyelorenal back flow and may produce iodine medicated thyrotropic effects described under PRECAUTIONS.

INDICATIONS AND USAGE

Cysto-Conray II is indicated for use in retrograde cystography and cystourethrography.

CONTRAINDICATIONS

See WARNINGS concerning inadvertant intrathecal administration.

WARNINGS

SEVERE ADVERSE EVENTS – INADVERTENT INTRATHECAL ADMINISTRATION: Serious adverse reactions have been reported due to the inadvertent intrathecal administration of iodinated contrast media that are not indicated for intrathecal use. These serious adverse reactions include: death, convulsions, cerebral hemorrhage, coma, paralysis, arachnoiditis, acute renal failure, cardiac arrest, seizures, rhabdomyolysis, hyperthermia, and brain edema. Special attention must be given to ensure that this drug product is not administered intrathecally.

PRECAUTIONS

General

Diagnostic procedures which involve the use of radiopaque diagnostic agents should be carried out under the direction of personnel with the prerequisite training and with a thorough knowledge of the particular procedure to be performed. Appropriate facilities should be available for coping with any complication of the procedure, as well as for emergency treatment of severe reactions to the contrast agent itself. After administration of the radiocontrast agent, competent personnel and emergency facilities should be available for at least 30 to 60 minutes since delayed reactions have occurred (see ADVERSE REACTIONS).

The possibility of an idiosyncratic reaction in susceptible patients should always be considered (see ADVERSE REACTIONS). The susceptible population includes patients with a history of a previous reaction to a contrast medium, patients with a known sensitivity to iodine per se and patients with a known clinical hypersensitivity: bronchial asthma, hay fever and food allergies.

A positive history of allergies or hypersensitivity does not arbitrarily contraindicate the use of a contrast agent where a diagnostic procedure is thought essential, but caution should be exercised (see ADVERSE REACTIONS). Premedication with antihistamines or corticosteroids to avoid or minimize possible allergic reactions in such patients should be considered. Recent reports indicate that such pre-treatment does not prevent serious life-threatening reactions, but may reduce both their incidence and severity.

Since these procedures require instrumentation, special precautions should be observed in those patients known to have an acute urinary tract infection.

Filling of the bladder should be done at a steady rate, exercising caution to avoid excessive pressure. Sterile procedures should be employed in administration.

Carcinogenesis, Mutagenesis, Impairment of Fertility

No long-term animal studies have been performed to evaluate carcinogenic potential, mutagenic potential or whether this drug affects fertility in males or females.

Use in Pregnancy

Category C. Animal reproduction studies have not been conducted with Cysto-Conray II. It is also not known whether this drug can cause fetal harm when administered to a pregnant woman or can affect reproduction capacity. Cysto-Conray II should be used in pregnant women only if clearly needed.

Nursing Mothers

Iothalamate salts are excreted unchanged in human milk. Although it has not been established that serious adverse reactions occur in nursing infants, because of the potential for adverse reactions, caution should be exercised when Cysto-Conray II is administered to a nursing woman.

Information for the Patient

Patients receiving diagnostic agents for instillation urography should be instructed to:

1. Inform your physician if you are pregnant.
2. Inform your physician if you are allergic to any food, drugs or dyes used for x-ray procedures (see PRECAUTIONS, General).
3. Consult with your physician if, at some future date, any thyroid tests are planned. The iodine in this agent may interfere with later thyroid tests.
4. Inform your physician about any other medications you are currently taking.

Drug/Laboratory Test Interaction

Thyroid Function Tests – If indicated, these tests generally should be performed prior to the administration of any iodinated agent. However, thyroid function can be evaluated after use of these agents by using T3 resin uptake or free thyroxine assays.

ADVERSE REACTIONS

Irritation of the bladder or ureter, common to some degree to all contrast media administered for retrograde urographic procedures, may occasionally occur.

As with all contrast media, intravasation may lead to hypersensitivity reactions such as a sense of warmth, flushing, sneezing, sweating, chills, fever, urticaria, laryngeal edema, bronchospasm, hypertension, hypotension, cardiac arrhythmias and cardiac arrest.

Adverse reactions associated with procedural technique include injury to the urethra, bladder, ureter, and introduction of infection.

In the event of serious or anaphylactoid reactions, it should be kept in mind that the reactions known to occur with intravenous administration of radiopaque contrast materials are possible.

DOSAGE AND ADMINISTRATION

Patient Preparation

Unless contraindicated, an appropriate laxative is given the night before the examination.

Radiographic Technique

The radiographic procedure normally employed for cystography and cystourethrography should be employed. A preliminary radiograph is recommended before the contrast agent is administered.

Administration

Sterile catherization is essential. Cysto-Conray II may be introduced by gravity flow using an appropriate venoclysis set or by syringe. Excessive pressure should be avoided with any method of administration.

Usual Dosage

Cystography and Cystourethrography – Either Conray 43 supplied at 43% w/v or Cysto-Conray II supplied at a 17.2% w/v concentration may be used for these procedures. The desired concentration will vary depending upon the patient’s size and age and also with the technique and equipment used. (SEE CONRAY 43 PACKAGE INSERT FOR SPECIFIC INFORMATION ABOUT THE USE OF THIS PRODUCT.) Sufficient volume of contrast medium is administered to adequately fill the urinary bladder. The volume of solution required will vary depending upon the individual patient. Adults usually require a volume in the range of 200 to 400 mL. Children require a volume in proportion to their body size. The usual dose ranges from 30 to 300 mL.

HOW SUPPLIED

Cysto-Conray® II Glass Bottles | NDC Number
12 x 250 mL single dose bottles | 0019-0862-50

Storage

Store at 20° to 25°C (68° to 77°F) [see USP Controlled Room Temperature]. Exposing this product to very cold temperatures may result in crystallization of the salt. If this occurs, the containers should be brought to room temperature. Shake vigorously to assure complete dissolution of any crystals. The speed of dissolution may be increased by heating with circulating warm air. Before use, examine the product to assure that all solids are redissolved and that the container and closure have not been damaged.

This product is sensitive to light and must be protected from strong daylight or direct exposure to the sun.

As with all contrast media, the containers should be inspected prior to use to ensure that breakage or other damage has not occurred during shipping and handling. All containers should be inspected for closure integrity. Damaged containers should not be used.

Manufactured by:
Liebel-Flarsheim Company LLC
Raleigh, NC 27616

Made in USA

GBT 0862A0817
Revised 08/17

Guerbet

PACKAGE LABEL - PRINCIPAL DISPLAY PANEL - Cysto-Conray™ll Label

Not For Intravascular Administration
Sterile Solution

Cysto-Conray® ll
250 mL
NDC 0019-0862-50

Iothalamate Meglumine Injection USP 17.2%
81 mg/mL Organically Bound Iodine
For Retrograde Cystography and Cystourethrography

NOT FOR INTRATHECAL USE
Rx Only

Protect from light • Store at 20° to 25°C (68° to 77°F) [see USP Controlled Room Temperature].
Each mL contains 172 mg iothalamate meglumine, 0.110 mg edetate calcium disodium as a stabilizer, and 0.115 mg monobasic sodium phosphate as a buffer.
Single dose container • Discard unused portion
Usual Dosage: See Package Insert.

10230419

Guerbet

Manufactured by:
Liebel-Flarsheim Company LLC
Raleigh, NC 27616

Made in USA